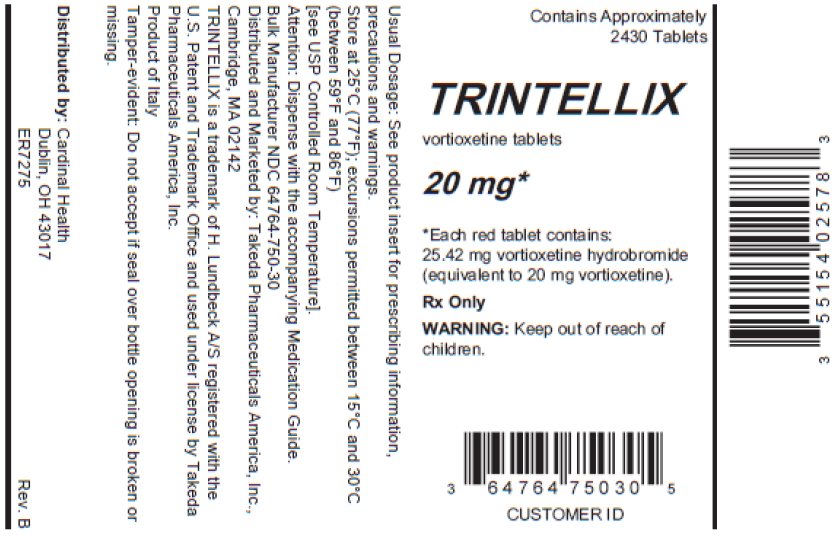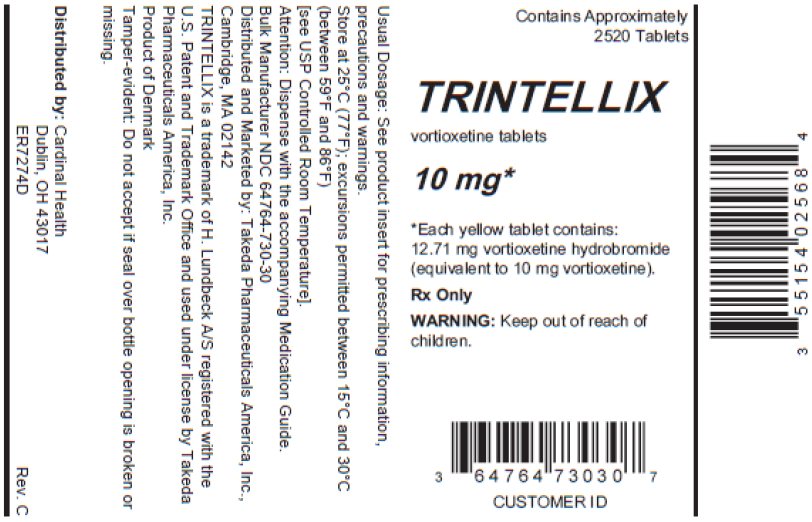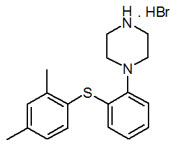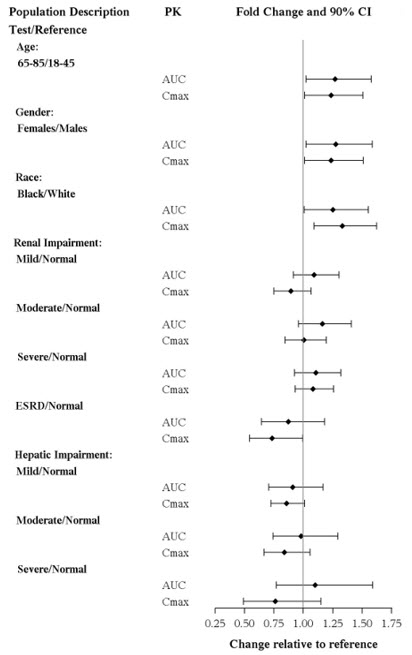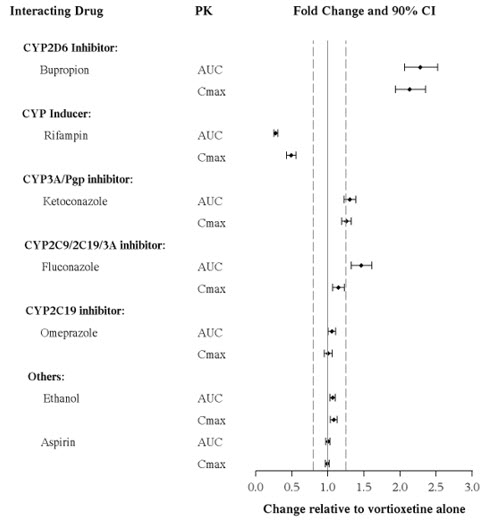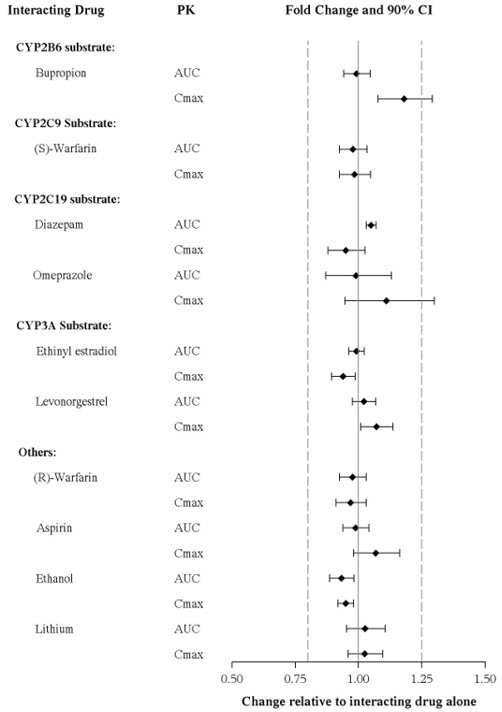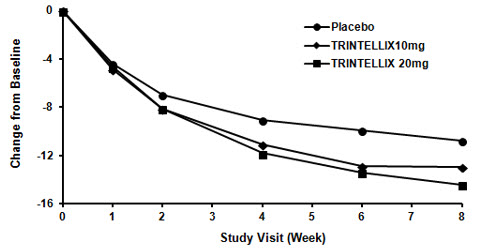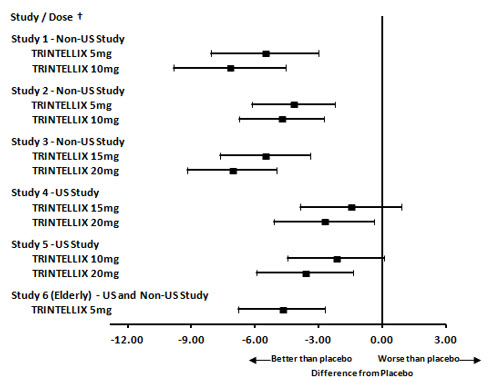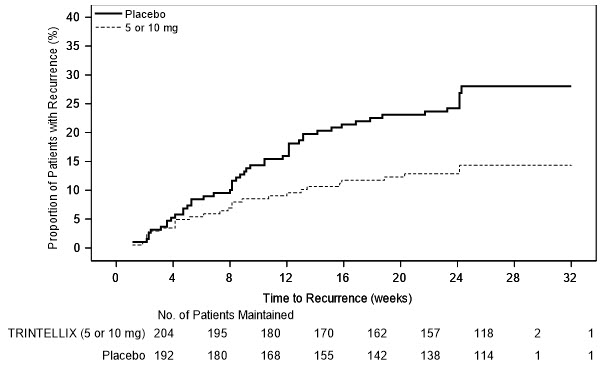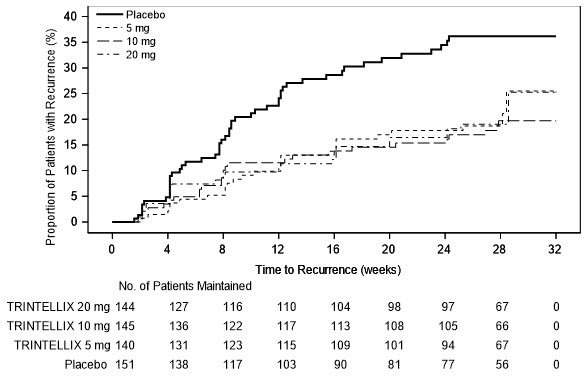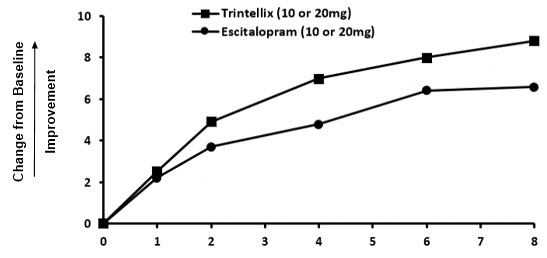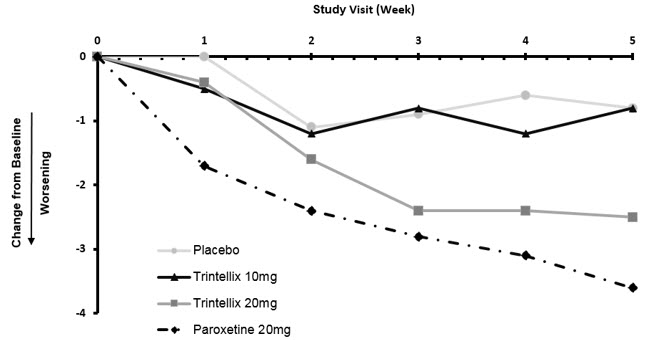 DRUG LABEL: Trintellix
NDC: 55154-0256 | Form: TABLET, FILM COATED
Manufacturer: Cardinal Health 107, LLC
Category: prescription | Type: HUMAN PRESCRIPTION DRUG LABEL
Date: 20260217

ACTIVE INGREDIENTS: VORTIOXETINE HYDROBROMIDE 10 mg/1 1
INACTIVE INGREDIENTS: MANNITOL; MICROCRYSTALLINE CELLULOSE; HYDROXYPROPYL CELLULOSE (90000 WAMW); SODIUM STARCH GLYCOLATE TYPE A POTATO; MAGNESIUM STEARATE; HYPROMELLOSE 2910 (6 MPA.S); TITANIUM DIOXIDE; POLYETHYLENE GLYCOL 400; FERRIC OXIDE YELLOW

HIGHLIGHTS OF PRESCRIBING INFORMATION

These highlights do not include all the information needed to use TRINTELLIX® safely and effectively. See full prescribing information for TRINTELLIX.
TRINTELLIX (vortioxetine) tablets, for oral use
Initial U.S. Approval: 2013

WARNING: SUICIDAL THOUGHTS AND BEHAVIORS

See full prescribing information for complete boxed warning.

- Increased risk of suicidal thinking and behavior in pediatric and young adult patients taking antidepressants.
- Closely monitor for worsening and emergence of suicidal thoughts and behaviors (5.1).
- TRINTELLIX is not approved for use in pediatric patients (8.4).

1 INDICATIONS AND USAGE

TRINTELLIX is indicated for the treatment of major depressive disorder (MDD) in adults (1, 14).

2 DOSAGE AND ADMINISTRATION

- The recommended starting dose is 10 mg administered orally once daily without regard to meals (2.1).
- The dose should then be increased to 20 mg/day, as tolerated (2.1).
- Consider 5 mg/day for patients who do not tolerate higher doses (2.1).
- TRINTELLIX can be discontinued abruptly. However, it is recommended that doses of 15 mg/day or 20 mg/day be reduced to 10 mg/day for one week prior to full discontinuation if possible (2.3).
- The maximum recommended dose is 10 mg/day in known CYP2D6 poor metabolizers (2.5).

3 DOSAGE FORMS AND STRENGTHS

Tablets: 5 mg, 10 mg, and 20 mg (3).

4 CONTRAINDICATIONS

- Hypersensitivity to vortioxetine or any components of the TRINTELLIX formulation (4).
- Monoamine Oxidase Inhibitors (MAOIs): Do not use MAOIs intended to treat psychiatric disorders with TRINTELLIX or within 21 days of stopping treatment with TRINTELLIX. Do not use TRINTELLIX within 14 days of stopping an MAOI intended to treat psychiatric disorders. In addition, do not start TRINTELLIX in a patient who is being treated with linezolid or intravenous methylene blue (4).

5 WARNINGS AND PRECAUTIONS

- Serotonin Syndrome: Increased risk when coadministered with other serotonergic agents, but also when taken alone. If it occurs, discontinue TRINTELLIX and serotonergic agents and initiate supportive measures (5.2).
- Increased Risk of Bleeding: Concomitant use of aspirin, nonsteroidal anti-inflammatory drugs, other antiplatelet drugs, warfarin, or other drugs that affect coagulation may increase risk (5.3).
- Activation of Mania/Hypomania: Screen patients for bipolar disorder (5.4).
- Angle Closure Glaucoma: Angle closure glaucoma has occurred in patients with untreated anatomically narrow angles treated with antidepressants (5.6).
- Hyponatremia: Can occur in association with the syndrome of inappropriate antidiuretic hormone secretion (SIADH) (5.7).
- Sexual Dysfunction: TRINTELLIX may cause symptoms of sexual dysfunction (5.8).

6 ADVERSE REACTIONS

Most common adverse reactions (incidence ≥5% and at least twice the rate of placebo) were: nausea, constipation and vomiting (6).

To report SUSPECTED ADVERSE REACTIONS, contact Takeda Pharmaceuticals America, Inc. at 1-877-TAKEDA-7 (1-877-825-3327) or FDA at 1-800-FDA-1088 or www.fda.gov/medwatch.

7 DRUG INTERACTIONS

- Strong inhibitors of CYP2D6: Reduce TRINTELLIX dose by half when coadministered (2.5, 7.1).
- Strong CYP Inducers: Consider dose increase of TRINTELLIX dose when coadministered for more than 14 days. The maximum recommended dose should not exceed 3 times the original dose (2.6, 7.1).

8 USE IN SPECIFIC POPULATIONS

Pregnancy: Third trimester use may increase risk for persistent pulmonary hypertension and withdrawal in the newborn (8.1).

FULL PRESCRIBING INFORMATION

WARNING: SUICIDAL THOUGHTS AND BEHAVIORS

Antidepressants increased the risk of suicidal thoughts and behavior in pediatric and young adult patients in short-term studies. Closely monitor all antidepressant-treated patients for clinical worsening, and for emergence of suicidal thoughts and behaviors [see Warnings and Precautions (5.1)]. TRINTELLIX is not approved for use in pediatric patients [see Use in Specific Populations (8.4)].

1 INDICATIONS AND USAGE

TRINTELLIX is indicated for the treatment of major depressive disorder (MDD) in adults.

2 DOSAGE AND ADMINISTRATION

2.1 Recommended Dosage

The recommended starting dose is 10 mg administered orally once daily without regard to meals. Dosage should then be increased to 20 mg/day, as tolerated. The efficacy and safety of doses above 20 mg/day have not been evaluated in controlled clinical trials. A dose decrease down to 5 mg/day may be considered for patients who do not tolerate higher doses [see Clinical Studies (14)].

2.2 Screen for Bipolar Disorder Prior to Starting TRINTELLIX

Prior to initiating treatment with TRINTELLIX or another antidepressant, screen patients for personal or family history of bipolar disorder, mania, or hypomania [see Warnings and Precautions (5.4)].

2.3 Discontinuing Treatment

Although TRINTELLIX can be abruptly discontinued, in placebo-controlled trials patients experienced transient adverse reactions such as headache and muscle tension following abrupt discontinuation of TRINTELLIX 15 mg/day or 20 mg/day. It is recommended that the dose be decreased to 10 mg/day for one week before full discontinuation of TRINTELLIX 15 mg/day or 20 mg/day [see Warnings and Precautions (5.5) and Adverse Reactions (6)].

2.4 Switching a Patient to or From a Monoamine Oxidase Inhibitor (MAOI) Intended to Treat Psychiatric Disorders

At least 14 days must elapse between discontinuation of a MAOI intended to treat psychiatric disorders and initiation of therapy with TRINTELLIX to avoid the risk of Serotonin Syndrome [see Warnings and Precautions (5.2)]. Conversely, at least 21 days must elapse after stopping TRINTELLIX before starting an MAOI intended to treat psychiatric disorders [see Contraindications (4)].

2.5 Use of TRINTELLIX in Known CYP2D6 Poor Metabolizers or in Patients Taking Strong CYP2D6 Inhibitors

The maximum recommended dose of TRINTELLIX is 10 mg/day in known CYP2D6 poor metabolizers. Reduce the dose of TRINTELLIX by one-half when patients are receiving a CYP2D6 strong inhibitor (e.g., bupropion, fluoxetine, paroxetine, or quinidine) concomitantly. The dose should be increased to the original level when the CYP2D6 inhibitor is discontinued [see Drug Interactions (7.1), Use in Specific Populations (8.6)].

2.6 Use of TRINTELLIX in Patients Taking Strong CYP Inducers

Consider increasing the dose of TRINTELLIX when a strong CYP inducer (e.g., rifampin, carbamazepine, or phenytoin) is coadministered for greater than 14 days. The maximum recommended dose should not exceed three times the original dose. The dose of TRINTELLIX should be reduced to the original level within 14 days, when the inducer is discontinued [see Drug Interactions (7.1)].

3 DOSAGE FORMS AND STRENGTHS

TRINTELLIX is available as:

- 5 mg: pink, almond shaped biconvex film coated tablet, debossed with "5" on one side and "TL" on the other side
- 10 mg: yellow, almond shaped biconvex film coated tablet, debossed with "10" on one side and "TL" on the other side
- 20 mg: red, almond shaped biconvex film coated tablet, debossed with "20" on one side and "TL" on the other side

4 CONTRAINDICATIONS

- Hypersensitivity to vortioxetine or any component of the formulation. Hypersensitivity reactions including anaphylaxis, angioedema, and urticaria have been reported in patients treated with TRINTELLIX [see Adverse Reactions (6.2)].
- The use of MAOIs intended to treat psychiatric disorders with TRINTELLIX or within 21 days of stopping treatment with TRINTELLIX is contraindicated because of an increased risk of serotonin syndrome. The use of TRINTELLIX within 14 days of stopping an MAOI intended to treat psychiatric disorders is also contraindicated [see Dosage and Administration (2.4), Warnings and Precautions (5.2)].
  Starting TRINTELLIX in a patient who is being treated with MAOIs such as linezolid or intravenous methylene blue is also contraindicated because of an increased risk of serotonin syndrome [see Warnings and Precautions (5.2)].

5 WARNINGS AND PRECAUTIONS

5.1 Suicidal Thoughts and Behaviors in Adolescents and Young Adults

In pooled analyses of placebo-controlled trials of antidepressant drugs (SSRIs and other antidepressant classes) that included approximately 77,000 adult patients and 4,500 pediatric patients, the incidence of suicidal thoughts and behaviors in antidepressant-treated patients age 24 years and younger was greater than in placebo-treated patients. There was considerable variation in risk of suicidal thoughts and behaviors among drugs, but there was an increased risk identified in young patients for most drugs studied. There were differences in absolute risk of suicidal thoughts and behaviors across the different indications, with the highest incidence in patients with MDD. The drug-placebo differences in the number of cases of suicidal thoughts and behaviors per 1,000 patients treated are provided in Table 1.

Table 1: Risk Differences of the Number of Patients of Suicidal Thoughts and Behaviors in the Pooled Placebo-Controlled Trials of Antidepressants in Pediatric [TRINTELLIX is not approved for use in pediatric patients.] and Adult Patients
Age Range | Drug-Placebo Difference in Number of Patients with Suicidal Thoughts and Behaviors per 1000 Patients Treated
 | Increases Compared to Placebo
<18 years old | 14 additional patients
18 to 24 years old | 5 additional patients
 | Decreases Compared to Placebo
25 to 64 years old | 1 fewer patient
≥65 years old | 6 fewer patients

It is unknown whether the risk of suicidal thoughts and behaviors in adolescents and young adults extends to longer-term use, i.e., beyond four months. However, there is substantial evidence from placebo-controlled maintenance trials in adults with MDD that the use of antidepressants can delay the recurrence of depression and that depression itself is a risk factor for suicidal thoughts and behaviors.

Monitor all antidepressant-treated patients for all approved populations for clinical worsening and emergence of suicidal thoughts and behaviors, especially during the initial few months of drug therapy, and at times of dosage changes. Counsel family members or caregivers of patients to monitor for changes in behavior and to alert the healthcare provider. Consider changing the therapeutic regimen, including possibly discontinuing TRINTELLIX, in patients whose depression is persistently worse, or who are experiencing emergent suicidal thoughts and behaviors.

5.2 Serotonin Syndrome

Serotonergic antidepressants, including TRINTELLIX, can precipitate serotonin syndrome, a potentially life-threatening condition. The risk is increased with concomitant use of other serotonergic drugs (including triptans, tricyclic antidepressants, fentanyl, lithium, tramadol, tryptophan, meperidine, methadone, buspirone, amphetamines, and St. John's Wort) and with drugs that impair metabolism of serotonin, i.e., MAOIs [see Contraindications (4), Drug Interactions (7.1)]. Serotonin syndrome can also occur when these drugs are used alone.

Serotonin syndrome signs and symptoms may include mental status changes (e.g., agitation, hallucinations, delirium, and coma), autonomic instability (e.g., tachycardia, labile blood pressure, dizziness, diaphoresis, flushing, hyperthermia), neuromuscular symptoms (e.g., tremor, rigidity, myoclonus, hyperreflexia, incoordination), seizures, and gastrointestinal symptoms (e.g., nausea, vomiting, diarrhea).

The concomitant use of TRINTELLIX with MAOIs is contraindicated. In addition, do not initiate TRINTELLIX in a patient being treated with MAOIs such as linezolid or intravenous methylene blue. No reports involved the administration of methylene blue by other routes (such as oral tablets or local tissue injection). If it is necessary to initiate treatment with an MAOI such as linezolid or intravenous methylene blue in a patient taking TRINTELLIX, discontinue TRINTELLIX before initiating treatment with the MAOI [see Contraindications (4), Drug Interactions (7.1)].

Monitor all patients taking TRINTELLIX for the emergence of serotonin syndrome. Discontinue treatment with TRINTELLIX and any concomitant serotonergic agents immediately if the above symptoms occur, and initiate supportive symptomatic treatment. If concomitant use of TRINTELLIX with other serotonergic drugs is clinically warranted, inform patients of the increased risk for serotonin syndrome and monitor for symptoms.

5.3 Increased Risk of Bleeding

The use of drugs that interfere with serotonin reuptake inhibition, including TRINTELLIX, may increase the risk of bleeding events. Concomitant use of aspirin, nonsteroidal anti-inflammatory drugs (NSAIDs), warfarin, and other anticoagulants may add to this risk. Case reports and epidemiological studies (case-control and cohort design) have demonstrated an association between use of drugs that interfere with serotonin reuptake and the occurrence of gastrointestinal bleeding. Based on data from the published observational studies, exposure to SSRIs or SNRIs, particularly in the month before delivery, has been associated with a less than 2-fold increase in the risk of postpartum hemorrhage [see Use in Specific Populations (8.1)]. Bleeding events related to drugs that inhibit serotonin reuptake have ranged from ecchymosis, hematoma, epistaxis, and petechiae to life-threatening hemorrhages.

Inform patients about the increased risk of bleeding when TRINTELLIX is coadministered with NSAIDs, aspirin, or other drugs that affect coagulation or bleeding. For patients taking warfarin, carefully monitor coagulation indices when initiating, titrating, or discontinuing TRINTELLIX [see Drug Interactions (7.1)].

5.4 Activation of Mania/Hypomania

In patients with bipolar disorder, treating a depressive episode with TRINTELLIX or another antidepressant may precipitate a mixed/manic episode. Symptoms of mania/hypomania were reported in <0.1% of patients treated with TRINTELLIX in premarketing clinical studies. Prior to initiating treatment with TRINTELLIX, screen patients for any personal or family history of bipolar disorder, mania, or hypomania.

5.5. Discontinuation Syndrome

Adverse reactions have been reported upon abrupt discontinuation of treatment with TRINTELLIX at doses of 15 mg/day and 20 mg/day [see Adverse Reactions (6.1)]. A gradual reduction in dosage rather than abrupt cessation is recommended whenever possible [see Dosage and Administration (2.3)].

Adverse reactions after discontinuation of serotonergic antidepressants, particularly after abrupt discontinuation include: nausea, sweating, dysphoric mood, irritability, agitation, dizziness, sensory disturbances (e.g., paresthesia, such as electric shock sensations), tremor, anxiety, confusion, headache, lethargy, emotional lability, insomnia, hypomania, tinnitus, and seizures.

5.6 Angle Closure Glaucoma

The pupillary dilation that occurs following use of many antidepressant drugs, including TRINTELLIX, may trigger an angle closure attack in a patient with anatomically narrow angles who does not have a patent iridectomy.

5.7 Hyponatremia

Hyponatremia has occurred as a result of treatment with serotonergic drugs, including TRINTELLIX. In many cases, hyponatremia appears to be the result of the syndrome of inappropriate antidiuretic hormone secretion (SIADH). One case with serum sodium lower than 110 mmol/L was reported in a subject treated with TRINTELLIX in a premarketing clinical study. Elderly patients may be at greater risk of developing hyponatremia with a serotonergic antidepressant. Also, patients taking diuretics or who are otherwise volume-depleted can be at greater risk. Discontinuation of TRINTELLIX in patients with symptomatic hyponatremia and appropriate medical intervention should be instituted. Signs and symptoms of hyponatremia include headache, difficulty concentrating, memory impairment, confusion, weakness, and unsteadiness, which can lead to falls. More severe and/or acute cases have included hallucination, syncope, seizure, coma, respiratory arrest, and death.

5.8 Sexual Dysfunction

Use of serotonergic antidepressants, including TRINTELLIX, may cause symptoms of sexual dysfunction [see Adverse Reactions (6.1)]. In male patients, serotonergic antidepressant use may result in ejaculatory delay or failure, decreased libido, and erectile dysfunction. In female patients, use may result in decreased libido and delayed or absent orgasm.

It is important for prescribers to inquire about sexual function prior to initiation of TRINTELLIX and to inquire specifically about changes in sexual function during treatment, because sexual function may not be spontaneously reported. When evaluating changes in sexual function, obtaining a detailed history (including timing of symptom onset) is important because sexual symptoms may have other causes, including the underlying psychiatric disorder. Discuss potential management strategies to support patients in making informed decisions about treatment.

6 ADVERSE REACTIONS

The following adverse reactions are discussed in greater detail in other sections of the label.

- Hypersensitivity [see Contraindications (4)]
- Clinical Worsening and Suicide Risk [see Warnings and Precautions (5.1)]
- Serotonin Syndrome [see Warnings and Precautions (5.2)]
- Increased Risk of Bleeding [see Warnings and Precautions (5.3)]
- Activation of Mania/Hypomania [see Warnings and Precautions (5.4)]
- Discontinuation Syndrome [see Warnings and Precautions (5.5)]
- Angle Closure Glaucoma [see Warnings and Precautions (5.6)]
- Hyponatremia [see Warnings and Precautions (5.7)]

6.1 Clinical Studies Experience

Because clinical trials are conducted under widely varying conditions, adverse reaction rates observed in the clinical trials of a drug cannot be directly compared to rates in the clinical trials of another drug and may not reflect the rates observed in clinical practice.

Patient Exposure

TRINTELLIX was evaluated for safety in 5,852 patients (18 years to 88 years of age) diagnosed with MDD who participated in pre- and postmarketing clinical studies; 2,616 of those patients were exposed to TRINTELLIX in 6 to 8 week, placebo-controlled studies at doses ranging from 5 mg to 20 mg once daily; 204 patients were exposed to TRINTELLIX in a 24 to 64 week placebo-controlled maintenance study at doses of 5 mg to 10 mg once daily; and 429 patients were exposed to TRINTELLIX in a 32 week placebo-controlled maintenance study in the U.S. at doses of 5 mg, 10 mg, and 20 mg, once daily. Patients from the 6 to 8 week studies continued into 12-month open-label studies. A total of 2,586 patients were exposed to at least one dose of TRINTELLIX in open-label studies, 1,727 were exposed to TRINTELLIX for 6 months and 885 were exposed for at least 1 year.

Adverse Reactions Reported as Reasons for Discontinuation of Treatment

In pooled 6 to 8 week placebo-controlled studies the incidence of patients who received TRINTELLIX 5 mg/day, 10 mg/day, 15 mg/day, and 20 mg/day and discontinued treatment because of an adverse reaction was 5%, 6%, 8%, and 8%, respectively, compared to 4% of placebo-treated patients. Nausea was the most common adverse reaction reported as a reason for discontinuation.

Common Adverse Reactions in Placebo-Controlled MDD Studies

The most commonly observed adverse reactions in MDD patients treated with TRINTELLIX in 6 to 8 week placebo-controlled studies (incidence ≥5% and at least twice the rate of placebo) were nausea, constipation and vomiting.

Table 2 shows the incidence of common adverse reactions that occurred in ≥2% of MDD patients treated with any TRINTELLIX dose and at least 2% more frequently than in placebo-treated patients in the 6 to 8 week placebo-controlled studies.

Table 2: Adverse Reactions Occurring in ≥2% of Patients Treated with Any TRINTELLIX Dose and at Least 2% Greater Than the Incidence in Placebo-Treated Patients
System Organ Class Preferred Term | TRINTELLIX 5 mg/day | TRINTELLIX 10 mg/day | TRINTELLIX 15 mg/day | TRINTELLIX 20 mg/day | Placebo
System Organ Class Preferred Term | N=1013 % | N=699 % | N=449 % | N=455 % | N=1621 %
Gastrointestinal disorders
Nausea | 21 | 26 | 32 | 32 | 9
Diarrhea | 7 | 7 | 10 | 7 | 6
Dry mouth | 7 | 7 | 6 | 8 | 6
Constipation | 3 | 5 | 6 | 6 | 3
Vomiting | 3 | 5 | 6 | 6 | 1
Flatulence | 1 | 3 | 2 | 1 | 1
Nervous system disorders
Dizziness | 6 | 6 | 8 | 9 | 6
Psychiatric disorders
Abnormal dreams | <1 | <1 | 2 | 3 | 1
Skin and subcutaneous tissue disorders
Pruritus [includes pruritus generalized] | 1 | 2 | 3 | 3 | 1

Nausea

Nausea was the most common adverse reaction and its frequency was dose-related (Table 2). It was usually considered mild or moderate in intensity and the median duration was two weeks. Nausea was more common in females than males. Nausea most commonly occurred in the first week of TRINTELLIX treatment with 15 to 20% of patients experiencing nausea after one to two days of treatment. Approximately 10% of patients taking TRINTELLIX 10 mg/day to 20 mg/day had nausea at the end of the 6 to 8 week placebo-controlled studies.

Sexual Dysfunction

Difficulties in sexual desire, sexual performance and sexual satisfaction often occur as manifestations of psychiatric disorders or comorbid conditions, but they may also be consequences of pharmacologic treatment, including TRINTELLIX. In addition to the data from the MDD studies mentioned below, TRINTELLIX has been prospectively assessed for its effects in MDD patients with existing TESD induced by prior SSRI treatment and in healthy adults with normal sexual function at baseline [see Clinical Studies (14)].

Voluntarily Reported Adverse Reactions of Sexual Dysfunction

In the MDD 6 to 8 week controlled trials of TRINTELLIX, voluntarily reported adverse reactions related to sexual dysfunction were captured as individual event terms. These event terms have been aggregated and the overall incidence was as follows. In male patients the overall incidence was 3%, 4%, 4%, 5% in TRINTELLIX 5 mg/day, 10 mg/day, 15 mg/day, 20 mg/day, respectively, compared to 2% in placebo. In female patients, the overall incidence was <1%, 1%, <1%, 2% in TRINTELLIX 5 mg/day, 10 mg/day, 15 mg/day, 20 mg/day, respectively, compared to <1% in placebo.

Adverse Reactions of Sexual Dysfunction in Patients with Normal Sexual Functioning at Baseline

Because voluntarily reported adverse sexual reactions are known to be underreported, in part because patients and physicians may be reluctant to discuss them, the Arizona Sexual Experiences Scale (ASEX), a validated measure designed to identify sexual side effects, was used prospectively in seven placebo-controlled trials. The ASEX scale includes five questions that pertain to the following aspects of sexual function: 1) sex drive, 2) ease of arousal, 3) ability to achieve erection (men) or lubrication (women), 4) ease of reaching orgasm, and 5) orgasm satisfaction.

The presence or absence of sexual dysfunction among patients entering clinical studies was based on their self-reported ASEX scores. For patients without sexual dysfunction at baseline (approximately 1/3 of the population across all treatment groups in each study), Table 3 shows the incidence of patients that developed TESD when treated with TRINTELLIX or placebo in any fixed dose group. Physicians should routinely inquire about possible sexual side effects.

Table 3: ASEX Incidence of Treatment Emergent Sexual Dysfunction [Incidence based on number of subjects with sexual dysfunction during the study/number of subjects without sexual dysfunction at baseline. Sexual dysfunction was defined as a subject scoring any of the following on the ASEX scale at two consecutive visits during the study: 1) total score ≥19; 2) any single item ≥5; 3) three or more items each with a score ≥4]
 | TRINTELLIX 5 mg/day N=65:67 [Sample size for each dose group is the number of patients (females:males) without sexual dysfunction at baseline] | TRINTELLIX 10 mg/day N=94:86 | TRINTELLIX 15 mg/day N=57:67 | TRINTELLIX 20 mg/day N=67:59 | Placebo N=135:162
Females | 22% | 23% | 33% | 34% | 20%
Males | 16% | 20% | 19% | 29% | 14%

Adverse Reactions Following Abrupt Discontinuation of TRINTELLIX Treatment

Discontinuation symptoms have been prospectively evaluated in patients taking TRINTELLIX 10 mg/day, 15 mg/day, and 20 mg/day using the Discontinuation-Emergent Signs and Symptoms (DESS) scale in clinical trials. Some patients experienced discontinuation symptoms such as headache, muscle tension, mood swings, sudden outbursts of anger, dizziness, and runny nose in the first week of abrupt discontinuation of TRINTELLIX 15 mg/day and 20 mg/day.

Laboratory Tests

TRINTELLIX has not been associated with any clinically important changes in laboratory test parameters in serum chemistry (except sodium), hematology and urinalysis as measured in the 6 to 8 week placebo-controlled studies. Hyponatremia has been reported with the treatment of TRINTELLIX [see Warnings and Precautions (5.7)]. In the 6-month, double-blind, placebo-controlled phase of a long-term study in patients who had responded to TRINTELLIX during the initial 12 week, open-label phase, there were no clinically important changes in lab test parameters between TRINTELLIX and placebo-treated patients.

Weight

TRINTELLIX had no significant effect on body weight as measured by the mean change from baseline in the 6 to 8 week placebo-controlled studies. In the six month, double-blind, placebo-controlled phase of a long-term study in patients who had responded to TRINTELLIX during the initial 12-week, open-label phase, there was no significant effect on body weight between TRINTELLIX and placebo-treated patients.

Vital Signs

TRINTELLIX has not been associated with any clinically significant effects on vital signs, including systolic and diastolic blood pressure and heart rate, as measured in placebo-controlled studies.

Other Adverse Reactions Observed in Clinical Studies

The following listing does not include reactions: 1) already listed in previous tables or elsewhere in labeling, 2) for which a drug cause was remote, 3) which were so general as to be uninformative, 4) which were not considered to have significant clinical implications, or 5) which occurred at a rate equal to or less than placebo.

Ear and labyrinth disorders — vertigo

Gastrointestinal disorders — dyspepsia

Nervous system disorders — dysgeusia

Vascular disorders — flushing

6.2 Postmarketing Experience

The following adverse reactions have been identified during postapproval use of TRINTELLIX. Because these reactions are reported voluntarily from a population of uncertain size, it is not always possible to reliably estimate their frequency or establish a causal relationship to drug exposure.

Endocrine disorders — hyperprolactinemia

Gastrointestinal System — acute pancreatitis

Immune system disorders — hypersensitivity reactions (including anaphylaxis and urticaria)

Metabolic disorders — weight gain

Nervous system disorders — seizure, headache

Psychiatric disorders — aggression, agitation, anger, hostility, irritability

Respiratory, thoracic and mediastinal disorders — anosmia, hyposmia

Skin and subcutaneous tissue disorders — rash, generalized rash, hyperhidrosis

7 DRUG INTERACTIONS

7.1 Drugs Having Clinically Important Interactions with TRINTELLIX

Table 4: Clinically Important Drug Interactions with TRINTELLIX
Monoamine Oxidase Inhibitors (MAOIs)
Clinical Impact | The concomitant use of SSRIs and SNRIs including TRINTELLIX with MAOIs increases the risk of serotonin syndrome.
Intervention | Concomitant use of TRINTELLIX is contraindicated:; - With an MAOI intended to treat psychiatric disorders or within 21 days of stopping treatment with TRINTELLIX. - Within 14 days of stopping an MAOI intended to treat psychiatric disorders. - In a patient who is being treated with linezolid or intravenous methylene blue.; [see Dosage and Administration (2.4), Contraindications (4), Warnings and Precautions (5.2)]
Examples | selegiline, tranylcypromine, isocarboxazid, phenelzine, linezolid, methylene blue
Other Serotonergic Drugs
Clinical Impact | Concomitant use of TRINTELLIX with other serotonergic drugs increases the risk of serotonin syndrome.
Intervention | Monitor for symptoms of serotonin syndrome when TRINTELLIX is used concomitantly with other drugs that may affect the serotonergic neurotransmitter systems. If serotonin syndrome occurs, consider discontinuation of TRINTELLIX and/or concomitant serotonergic drugs [see Warnings and Precautions (5.2)].
Examples | Other SNRIs, SSRIs, triptans, tricyclic antidepressants, opioids, lithium, buspirone, amphetamines, tryptophan, and St. John's Wort
Strong Inhibitors of CYP2D6
Clinical Impact | Concomitant use of TRINTELLIX with strong CYP2D6 inhibitors increases plasma concentrations of vortioxetine.
Intervention | Reduce TRINTELLIX dose by half when a strong CYP2D6 inhibitor is coadministered [see Dosage and Administration (2.5)].
Examples | bupropion, fluoxetine, paroxetine, quinidine
Strong CYP Inducers
Clinical Impact | Concomitant use of TRINTELLIX with a strong CYP inducer decreases plasma concentrations of vortioxetine.
Intervention | Consider increasing the TRINTELLIX dose when a strong CYP inducer is coadministered. The maximum dose is not recommended to exceed three times the original dose [see Dosage and Administration (2.6)].
Examples | rifampin, carbamazepine, phenytoin
Drugs that Interfere with Hemostasis (antiplatelets agents and anticoagulants)
Clinical Impact | Concomitant use of TRINTELLIX with an antiplatelet or anticoagulant drug may potentiate the risk of bleeding.
Intervention | Inform patients of the increased risk of bleeding associated with the concomitant use of TRINTELLIX and antiplatelet agents and anticoagulants. For patients taking warfarin, carefully monitor the international normalized ratio [see Warnings and Precautions (5.3), Drug Interactions (7.2)].
Examples | aspirin, clopidogrel, heparin, warfarin
Drugs Highly Bound to Plasma Protein
Clinical Impact | TRINTELLIX is highly bound to plasma protein. The concomitant use of TRINTELLIX with another drug that is highly bound to plasma protein may increase free concentrations of TRINTELLIX or other tightly-bound drugs in plasma.
Intervention | Monitor for adverse reactions and reduce dosage of TRINTELLIX or other protein bound drugs as warranted [see Drug Interactions (7.2)].
Examples | Warfarin

7.2 Effect of TRINTELLIX on Other Drugs

Other CNS Active Agents

No clinically relevant effect was observed on steady-state lithium exposure following coadministration with multiple daily doses of TRINTELLIX. Multiple doses of TRINTELLIX did not affect the pharmacokinetics or pharmacodynamics (composite cognitive score) of diazepam [see Clinical Pharmacology (12.3)].

A clinical study has shown that TRINTELLIX (single dose of 20 or 40 mg) did not increase the impairment of mental and motor skills caused by alcohol (single dose of 0.6 g/kg) [see Clinical Pharmacology (12.3)].

Drugs That Interfere with Hemostasis

Following coadministration of stable doses of warfarin (1 to 10 mg/day) with multiple daily doses of TRINTELLIX, no significant effects were observed in INR, prothrombin values or total warfarin (protein bound plus free drug) pharmacokinetics for both R- and S-warfarin. Coadministration of aspirin 150 mg/day with multiple daily doses of TRINTELLIX had no significant inhibitory effect on platelet aggregation or pharmacokinetics of aspirin and salicylic acid [see Clinical Pharmacology (12.3)]. Patients receiving other drugs that interfere with hemostasis should be carefully monitored when TRINTELLIX is initiated or discontinued [see Warnings and Precautions (5.3), Drug Interactions (7.1)].

Highly Protein Bound Drugs

In a clinical study with coadministration of TRINTELLIX (10 mg/day) and warfarin (1 mg/day to 10 mg/day), a highly protein bound drug, no significant change in INR was observed [see Drug Interactions (7.1), Clinical Pharmacology (12.3)].

7.3 Interference with Urine Enzyme Immunoassays for Methadone

False positive results in urine enzyme immunoassays for methadone have been reported in patients who have taken vortioxetine. An alternative analytical technique (e.g., chromatographic methods) should be considered to confirm positive methadone urine drug screen results.

8 USE IN SPECIFIC POPULATIONS

8.1 Pregnancy

Pregnancy Exposure Registry

There is a pregnancy exposure registry that monitors pregnancy outcomes in women exposed to antidepressants during pregnancy. Healthcare providers are encouraged to register patients by calling the National Pregnancy Registry for Antidepressants at 1-844-405-6185 or visiting online at https://womensmentalhealth.org/clinical-and-research-programs/pregnancyregistry/antidepressants/.

Risk Summary

Based on data from published observational studies, exposure to SSRIs or SNRIs, particularly in the month before delivery, has been associated with a less than 2-fold increase in the risk of postpartum hemorrhage [see Warnings and Precautions (5.3) and Clinical Considerations].

There are limited human data on TRINTELLIX use during pregnancy to inform any drug-associated risks. However, there are clinical considerations regarding neonates exposed to SSRIs and SNRIs, including TRINTELLIX, during the third trimester of pregnancy [see Clinical Considerations]. Vortioxetine administered to pregnant rats and rabbits during the period of organogenesis at doses ≥15 times and 10 times the maximum recommended human dose (MRHD), respectively, resulted in decreased fetal body weight and delayed ossification. No malformations were seen at doses up to 77 times and 58 times the MRHD, respectively. Vortioxetine administered to pregnant rats during gestation and lactation at oral doses ≥20 times the MRHD resulted in a decrease in the number of live-born pups and an increase in early postnatal pup mortality. Decreased pup weight at birth to weaning occurred at 58 times the MRHD and delayed physical development occurred at ≥20 times the MRHD. These effects were not seen at 5 times the MRHD [see Data]. Advise a pregnant woman of the potential risk to a fetus.

The estimated background risk of major birth defects and miscarriage for the indicated population is unknown. All pregnancies have a background risk of birth defect, loss or other adverse outcomes. In the U.S. general population, the estimated background risk of major birth defects and miscarriage in clinically recognized pregnancies is 2-4% and 15-20%, respectively.

Clinical Considerations

Disease-associated Maternal and/or Embryo/Fetal Risk

A prospective, longitudinal study followed 201 pregnant women with a history of major depressive disorder who were euthymic and taking antidepressants at the beginning of pregnancy. The women who discontinued antidepressants during pregnancy were more likely to experience a relapse of major depression than women who continued antidepressants. Consider the risks of untreated depression when discontinuing or changing treatment with antidepressant medication during pregnancy and postpartum.

Fetal/Neonatal Adverse Reactions

Exposure to serotonergic antidepressants, including TRINTELLIX, in late pregnancy may lead to an increased risk for neonatal complications requiring prolonged hospitalization, respiratory support, and tube feeding, and/or persistent pulmonary hypertension of the newborn (PPHN). Monitor neonates who were exposed to TRINTELLIX in the third trimester of pregnancy for PPHN and drug discontinuation syndrome [see Data].

Maternal Adverse Reactions

Use of TRINTELLIX in the month before delivery may be associated with an increased risk of postpartum hemorrhage [see Warnings and Precautions (5.3)].

Data

Human Data

Third Trimester Exposure

Neonates exposed to SSRIs or SNRIs, late in the third trimester have developed complications requiring prolonged hospitalization, respiratory support and tube feeding. These findings are based on postmarketing reports. Such complications can arise immediately upon delivery. Reported clinical findings have included respiratory distress, cyanosis, apnea, seizures, temperature instability, feeding difficulty, vomiting, hypoglycemia, hypotonia, hypertonia, hyperreflexia, tremor, jitteriness, irritability and constant crying. These features are consistent with either a direct toxic effect of SSRIs and SNRIs or possibly, a drug discontinuation syndrome. In some cases, the clinical picture was consistent with serotonin syndrome [see Warnings and Precautions (5.2)].

Exposure during late pregnancy to SSRIs may have an increased risk for persistent pulmonary hypertension of the newborn (PPHN). PPHN occurs in one to two per 1,000 live births in the general population and is associated with substantial neonatal morbidity and mortality. In a retrospective case-control study of 377 women whose infants were born with PPHN and 836 women whose infants were born healthy, the risk for developing PPHN was approximately six fold higher for infants exposed to SSRIs after the 20th week of gestation compared to infants who had not been exposed to antidepressants during pregnancy. A study of 831,324 infants born in Sweden in 1997 - 2005 found a PPHN risk ratio of 2.4 (95% CI 1.2-4.3) associated with patient-reported maternal use of SSRIs "in early pregnancy" and a PPHN risk ratio of 3.6 (95% CI 1.2-8.3) associated with a combination of patient-reported maternal use of SSRIs "in early pregnancy" and an antenatal SSRI prescription "in later pregnancy."

Animal Data

In pregnant rats and rabbits, no malformations were seen when vortioxetine was given during the period of organogenesis at oral doses up to 160 and 60 mg/kg/day, respectively. These doses are 77 and 58 times the maximum recommended human dose (MRHD) of 20 mg on a mg/m^2 basis, in rats and rabbits, respectively. Developmental delay, seen as decreased fetal body weight and delayed ossification, occurred in rats and rabbits at doses equal to and greater than 30 and 10 mg/kg (15 and 10 times the MRHD, respectively) in the presence of maternal toxicity (decreased food consumption and decreased body weight gain). When vortioxetine was administered to pregnant rats at oral doses of 40 and 120 mg/kg (20 and 58 times the MRHD, respectively) throughout pregnancy and lactation, the number of live-born pups was decreased and early postnatal pup mortality was increased. Additionally, pup weights were decreased at birth to weaning at 120 mg/kg and development (specifically eye opening) was slightly delayed at 40 and 120 mg/kg. These effects were not seen at 10 mg/kg (5 times the MRHD).

8.2 Lactation

Risk Summary

There is no information regarding the presence of vortioxetine in human milk, the effects on the breastfed infant, or the effects on milk production. Vortioxetine is present in rat milk [see Data]. The developmental and health benefits of breastfeeding should be considered along with the mother's clinical need for TRINTELLIX and any potential adverse effects on the breastfed child from TRINTELLIX or from the underlying maternal condition.

Data

Animal Data

Administration of [^14C]-vortioxetine to lactating rats at an oral dose of 20 times the maximum recommended human dose (MRHD) of 20 mg on a mg/m^2 basis, resulted in drug-related material in milk secretion. Milk to plasma ratio in lactating rats was 1, 1.2, 0.5, and 0.5 at 2, 6, 24, and 72 hours post dose.

8.4 Pediatric Use

The safety and effectiveness of TRINTELLIX have not been established in pediatric patients.

The safety and efficacy of TRINTELLIX were evaluated in two randomized, double-blind, placebo- and active-controlled 8-week studies in pediatric patients with MDD, one in patients 7 to 11 years of age (N=540 randomized) and one in patients 12 to 17 years of age (N=616 randomized). The primary efficacy endpoint for both studies was the change from baseline to week 8 in the Children's Depression Rating Scale-Revised (CDRS-R) total score. The CDRS-R assesses the severity of depression and change in depressive symptoms in children and adolescents with depression. TRINTELLIX was not superior to placebo in either study. Patients from the controlled 8-week studies were eligible to enroll in a 6-month open-label extension study (N=662 treated). Across the three studies, the most commonly observed adverse reactions to TRINTELLIX in pediatric patients 7 to 17 years of age were generally similar to those observed in adults [see Adverse Reactions (6)].

Antidepressants, such as TRINTELLIX, increase the risk of suicidal thoughts and behaviors in pediatric patients [see Boxed Warning and Warnings and Precautions (5.1)].

Juvenile Animal Toxicity Data

Administration of vortioxetine to juvenile rats (oral doses of 10, 20, and 40 mg/kg/day twice daily from Postnatal Day 21 to 91) resulted in a neurobehavioral effect at the highest dose of 40 mg/kg twice daily (increased peak auditory startle amplitude) during the treatment period. The effect was not seen at the end of the recovery period. When animals were mated after the 4-week recovery period, viability was decreased in the offspring of mated pairs treated with 40 mg/kg twice daily. The no-observed adverse effect dose was 20 mg/kg twice daily based on both the neurobehavioral and reproductive effects. This dose was associated with plasma vortioxetine exposure (AUC) approximately 2 times that in pediatric patients.

8.5 Geriatric Use

No dose adjustment is recommended on the basis of age (Figure 1). Results from a single-dose pharmacokinetic study in elderly (>65 years old) vs young (24 to 45 years old) subjects demonstrated that the pharmacokinetics were generally similar between the two age groups.

Of the 2,616 subjects in clinical studies of TRINTELLIX, 11% (286) were 65 and over, which included subjects from a placebo-controlled study specifically in elderly patients [see Clinical Studies (14)]. No overall differences in safety or effectiveness were observed between these subjects and younger subjects, and other reported clinical experience has not identified differences in responses between the elderly and younger patients.

Serotonergic antidepressants have been associated with cases of clinically significant hyponatremia in elderly patients, who may be at greater risk for this adverse event [see Warnings and Precautions (5.7)].

8.6 CYP2D6 Poor Metabolizers

Dosage reduction is recommended in patients known to be poor CYP2D6 metabolizers because these patients have higher vortioxetine plasma concentrations than extensive CYP2D6 metabolizers [see Dosage and Administration (2.5) and Clinical Pharmacology (12.3)].

10 OVERDOSAGE

There is limited clinical trial experience regarding human overdosage with TRINTELLIX. In premarketing clinical studies, cases of overdose were limited to patients who accidentally or intentionally consumed up to a maximum dose of 40 mg of TRINTELLIX. The maximum single dose tested was 75 mg in men. Ingestion of TRINTELLIX in the dose range of 40 to 75 mg was associated with increased rates of nausea, dizziness, diarrhea, abdominal discomfort, generalized pruritus, somnolence, and flushing.

There have been postmarketing reports of overdoses of TRINTELLIX. The most frequently reported symptoms with overdoses up to 80 mg (four times the maximum recommended daily dose) were nausea and vomiting. With overdoses greater than 80 mg, a case of serotonin syndrome in combination with another serotonergic drug, and a case of seizure, have been reported.

No specific antidotes for TRINTELLIX are known. Consider contacting the Poison Help Line (1-800-222-1222) or a medical toxicologist for additional overdose management recommendations.

11 DESCRIPTION

TRINTELLIX is an immediate-release tablet for oral administration that contains the beta (β) polymorph of vortioxetine hydrobromide (HBr), an antidepressant. Vortioxetine HBr is known chemically as 1-[2-(2,4-Dimethyl-phenylsulfanyl)-phenyl]-piperazine, hydrobromide. The empirical formula is C18 H22 N2 S, HBr with a molecular weight of 379.36 g/mol. The structural formula is:

Vortioxetine HBr is a white to very slightly beige powder that is slightly soluble in water.

Each TRINTELLIX tablet contains 6.355 mg, 12.71 mg or 25.42 mg of vortioxetine HBr equivalent to 5 mg, 10 mg, or 20 mg of vortioxetine, respectively. The inactive ingredients in TRINTELLIX tablets include mannitol, microcrystalline cellulose, hydroxypropyl cellulose, sodium starch glycolate, magnesium stearate and film coating which consists of hypromellose, titanium dioxide, polyethylene glycol 400, iron oxide red (5 mg and 20 mg) and iron oxide yellow (10 mg).

12 CLINICAL PHARMACOLOGY

12.1 Mechanism of Action

The mechanism of the antidepressant effect of vortioxetine is not fully understood, but is thought to be related to its enhancement of serotonergic activity in the CNS through inhibition of the reuptake of serotonin (5-HT). It also has several other activities including 5-HT3 receptor antagonism and 5-HT1A receptor agonism. The contribution of these activities to vortioxetine's antidepressant effect has not been established.

12.2 Pharmacodynamics

Vortioxetine binds with high affinity to the human serotonin transporter (Ki=1.6 nM), but not to the norepinephrine (Ki=113 nM) or dopamine (Ki>1000 nM) transporters. Vortioxetine potently and selectively inhibits reuptake of serotonin (IC50=5.4 nM). Vortioxetine binds to 5-HT3 (Ki=3.7 nM), 5-HT1A (Ki=15 nM), 5-HT7 (Ki=19 nM), 5-HT1D (Ki=54 nM), and 5-HT1B (Ki=33 nM), receptors and is a 5-HT3, 5-HT1D, and 5-HT7 receptor antagonist, 5-HT1B receptor partial agonist, and 5-HT1A receptor agonist.

In humans, the mean 5-HT transporter occupancy, based on the results from two clinical PET studies using 5-HTT ligands ([^11C]-MADAM or [^11C]-DASB), was approximately 50% at 5 mg/day, 65% at 10 mg/day and approximately 80% at 20 mg/day in the regions of interest.

Effect on Cardiac Repolarization

The effect of vortioxetine 10 mg and 40 mg administered once daily on QTc interval was evaluated in a randomized, double-blind, placebo-, and active-controlled (moxifloxacin 400 mg), four-treatment-arm parallel study in 340 male subjects. In the study the upper bound of the one-sided 95% confidence interval for the QTc was below 10 ms, the threshold for regulatory concern. The oral dose of 40 mg is sufficient to assess the effect of metabolic inhibition.

Effect on Driving Performance

In a clinical study in healthy subjects, TRINTELLIX did not impair driving performance, or have adverse psychomotor or cognitive effects following single and multiple doses of 10 mg/day.

12.3 Pharmacokinetics

Vortioxetine pharmacological activity is due to the parent drug. The pharmacokinetics of vortioxetine (2.5 mg to 60 mg) are linear and dose-proportional when vortioxetine is administered once daily. The mean terminal half-life is approximately 66 hours, and steady-state plasma concentrations are typically achieved within two weeks of dosing.

Absorption

The maximal plasma vortioxetine concentration (Cmax) after dosing is reached within 7 to 11 hours postdose (Tmax). Steady-state mean Cmax values were 9, 18, and 33 ng/mL following doses of 5, 10, and 20 mg/day. Absolute bioavailability is 75%.

Effect of Food

No effect of food on the pharmacokinetics was observed.

Distribution

The apparent volume of distribution of vortioxetine is approximately 2600 L, indicating extensive extravascular distribution. The plasma protein binding of vortioxetine in humans is 98%, independent of plasma concentrations. No apparent difference in the plasma protein binding between healthy subjects and subjects with hepatic (mild, moderate or severe) or renal (mild, moderate, severe, ESRD) impairment is observed.

Elimination

Metabolism

Vortioxetine is extensively metabolized primarily through oxidation via cytochrome P450 isozymes CYP2D6, CYP3A4/5, CYP2C19, CYP2C9, CYP2A6, CYP2C8, and CYP2B6 and subsequent glucuronic acid conjugation. CYP2D6 is the primary enzyme catalyzing the metabolism of vortioxetine to its major, pharmacologically inactive, carboxylic acid metabolite, and poor metabolizers of CYP2D6 have approximately twice the vortioxetine plasma concentration of extensive metabolizers [see Dosage and Administration (2.5)].

Excretion

Following a single oral dose of [^14C]-labeled vortioxetine, approximately 59% and 26% of the administered radioactivity was recovered in the urine and feces, respectively as metabolites. Negligible amounts of unchanged vortioxetine were excreted in the urine up to 48 hours. The presence of hepatic (mild, moderate or severe) or renal impairment (mild, moderate, severe and ESRD) did not affect the apparent clearance of vortioxetine.

Specific Populations

No clinically significant differences in the exposures of vortioxetine were observed based on age, gender, ethnicity, renal function, or hepatic function.

The effects of intrinsic patient factors on the pharmacokinetics of vortioxetine are presented in Figure 1.

Figure 1. Impact of Intrinsic Factors on Vortioxetine PK

Drug Interaction Studies

Clinical Studies

Other Drugs on TRINTELLIX

The effects of other drugs on vortioxetine exposure are summarized in Figure 2.

Figure 2. Impact of Other Drugs on Vortioxetine PK

TRINTELLIX on Other Drugs

The effects of vortioxetine on the exposures of other drugs are summarized in Figure 3.

Figure 3. Impact of Vortioxetine on PK of Other Drugs

In Vitro

Vortioxetine and its metabolite(s) are unlikely to inhibit the following CYP enzymes and transporter based on in vitro data: CYP1A2, CYP2A6, CYP2B6, CYP2C8, CYP2C9, CYP2C19, CYP2D6, CYP2E1, CYP3A4/5, P-gp, BCRP, BSEP, MATE1, MATE2-K, OAT1, OAT3, OATP1B1, OATP1B3, OCT1, and OCT2. As such, no clinically relevant interactions with drugs metabolized/transported by these CYP enzymes or transporters would be expected.

In addition, vortioxetine did not induce CYP1A2, CYP2A6, CYP2B6, CYP2C8, CYP2C9, CYP2C19, and CYP3A4/5 in an in vitro study in cultured human hepatocytes. Chronic administration of TRINTELLIX is unlikely to induce the metabolism of drugs metabolized by these CYP isoforms. Furthermore, in a series of clinical drug interaction studies, coadministration of TRINTELLIX with substrates for CYP2B6 (e.g., bupropion), CYP2C9 (e.g., warfarin), and CYP2C19 (e.g., diazepam), had no clinical meaningful effect on the pharmacokinetics of these substrates.

13 NONCLINICAL TOXICOLOGY

13.1 Carcinogenesis, Mutagenesis, Impairment of Fertility

Carcinogenesis

Carcinogenicity studies were conducted in which CD-1 mice and Wistar rats were given oral doses of vortioxetine up to 50 and 100 mg/kg/day for male and female mice, respectively, and 40 and 80 mg/kg/day for male and female rats, respectively, for two years. The doses in the two species were approximately 12, 24, 20, and 39 times, respectively, the maximum recommended human dose (MRHD) of 20 mg on a mg/m^2 basis.

In rats, the incidence of benign polypoid adenomas of the rectum was statistically significantly increased in females at doses 39 times the MRHD, but not at 15 times the MRHD. These were considered related to inflammation and hyperplasia and possibly caused by an interaction with a vehicle component of the formulation used for the study. The finding did not occur in male rats at 20 times the MRHD.

In mice, vortioxetine was not carcinogenic in males or females at doses up to 12 and 24 times, respectively, the MRHD.

Mutagenicity

Vortioxetine was not genotoxic in the in vitro bacterial reverse mutation assay (Ames test), an in vitro chromosome aberration assay in cultured human lymphocytes, and an in vivo rat bone marrow micronucleus assay.

Impairment of Fertility

Treatment of rats with vortioxetine at doses up to 120 mg/kg/day had no effect on male or female fertility, which is 58 times the maximum recommended human dose (MRHD) of 20 mg on a mg/m^2 basis.

14 CLINICAL STUDIES

The efficacy of TRINTELLIX in treatment for MDD was established in six, 6 to 8 week randomized, double-blind, placebo-controlled, fixed-dose studies (including one study in the elderly) and one maintenance study in adult inpatients and outpatients who met the Diagnostic and Statistical Manual of Mental Disorders (DSM-IV-TR) criteria for MDD.

Adults (aged 18 years to 75 years)

The efficacy of TRINTELLIX in patients aged 18 years to 75 years was demonstrated in five, 6 to 8 week, placebo-controlled studies (Studies 1 to 5 in Table 5). In these studies, patients were randomized to TRINTELLIX 5 mg, 10 mg, 15 mg, or 20 mg or placebo once daily. For patients who were randomized to TRINTELLIX 15 mg/day or 20 mg/day, the final doses were titrated up from 10 mg/day after the first week.

The primary efficacy measures were the Hamilton Depression Scale (HAMD-24) total score in Study 2 and the Montgomery-Asberg Depression Rating Scale (MADRS) total score in all other studies. In each of these studies, at least one dose group of TRINTELLIX was superior to placebo in improvement of depressive symptoms as measured by mean change from baseline to endpoint visit on the primary efficacy measurement (see Table 5). Subgroup analysis by age, gender or race did not suggest any clear evidence of differential responsiveness. Two studies of the 5 mg dose in the U.S. (not represented in Table 5) failed to show effectiveness.

Elderly Study (aged 64 years to 88 years)

The efficacy of TRINTELLIX for the treatment of MDD was also demonstrated in a randomized, double-blind, placebo-controlled, fixed-dose study of TRINTELLIX in elderly patients (aged 64 years to 88 years) with MDD (Study 6 in Table 5). Patients meeting the diagnostic criteria for recurrent MDD with at least one previous major depressive episode before the age of 60 years and without comorbid cognitive impairment (Mini Mental State Examination score <24) received TRINTELLIX 5 mg or placebo.

Table 5: Primary Efficacy Results of 6 Week to 8 Week Clinical Trials
Study No. [Primary Measure] | Treatment Group | Number of Patients | Mean Baseline Score (SD) | LS Mean Change from Baseline (SE) | Placebo-subtracted Difference [Difference (drug minus placebo) in least-squares mean change from baseline.] (95% CI)
Study 1 [MADRS] Non-US Study | TRINTELLIX (5 mg/day) [Doses that are statistically significantly superior to placebo after adjusting for multiplicity.] | 108 | 34.1 (2.6) | -20.4 (1.0) | -5.9 (-8.6, -3.2)
Study 1 [MADRS] Non-US Study | TRINTELLIX (10 mg/day) | 100 | 34.0 (2.8) | -20.2 (1.0) | -5.7 (-8.5, -2.9)
Study 1 [MADRS] Non-US Study | Placebo | 105 | 33.9 (2.7) | -14.5 (1.0) | --
Study 2 [HAMD-24] Non-US Study | TRINTELLIX (5 mg/day) | 139 | 32.2 (5.0) | -15.4 (0.7) | -4.1 (-6.2, -2.1)
Study 2 [HAMD-24] Non-US Study | TRINTELLIX (10 mg/day) | 139 | 33.1 (4.8) | -16.2 (0.8) | -4.9 (-7.0, -2.9)
Study 2 [HAMD-24] Non-US Study | Placebo | 139 | 32.7 (4.4) | -11.3 (0.7) | --
Study 3 [MADRS] Non-US Study | TRINTELLIX (15 mg/day) | 149 | 31.8 (3.4) | -17.2 (0.8) | -5.5 (-7.7, -3.4)
Study 3 [MADRS] Non-US Study | TRINTELLIX (20 mg/day) | 151 | 31.2 (3.4) | -18.8 (0.8) | -7.1 (-9.2, -5.0)
Study 3 [MADRS] Non-US Study | Placebo | 158 | 31.5 (3.6) | -11.7 (0.8) | --
Study 4 [MADRS] US Study | TRINTELLIX (15 mg/day) | 145 | 31.9 (4.1) | -14.3 (0.9) | -1.5 (-3.9, 0.9)
Study 4 [MADRS] US Study | TRINTELLIX (20 mg/day) | 147 | 32.0 (4.4) | -15.6 (0.9) | -2.8 (-5.1, -0.4)
Study 4 [MADRS] US Study | Placebo | 153 | 31.5 (4.2) | -12.8 (0.8) | --
Study 5 [MADRS] US Study | TRINTELLIX (10 mg/day) | 154 | 32.2 (4.5) | -13.0 (0.8) | -2.2 (-4.5, 0.1)
Study 5 [MADRS] US Study | TRINTELLIX (20 mg/day) | 148 | 32.5 (4.3) | -14.4 (0.9) | -3.6 (-5.9, -1.4)
Study 5 [MADRS] US Study | Placebo | 155 | 32.0 (4.0) | -10.8 (0.8) | --
Study 6 (elderly) [HAMD-24] US and Non-US | TRINTELLIX (5 mg/day) | 155 | 29.2 (5.0) | -13.7 (0.7) | -3.3 (-5.3, -1.3)
Study 6 (elderly) [HAMD-24] US and Non-US | Placebo | 145 | 29.4 (5.1) | -10.3 (0.8) | --
SD: standard deviation; SE: standard error; LS Mean: least-squares mean; CI: unadjusted confidence interval.

TRINTELLIX was superior to placebo on the Clinical Global Impression of Improvement (CGI-I) scale, which is a clinician's impression of how much the patient's clinical condition has improved or worsened relative to baseline on a scale of 1 (very much improved) to 7 (very much worse).

Time Course of Treatment Response

In the 6 to 8 week placebo-controlled studies, an effect of TRINTELLIX based on the primary efficacy measure was generally observed starting at Week 2 and increased in subsequent weeks with the full antidepressant effect of TRINTELLIX generally not seen until Study Week 4 or later. Figure 4 depicts time course of response in U.S. based on the primary efficacy measure (MADRS) in Study 5.

Figure 4. Change from Baseline in MADRS Total Score by Study Visit (Week) in Study 5

Figure 5. Difference from Placebo in Mean Change from Baseline in MADRS Total Score at Week 6 or Week 8

† Results (point estimate and unadjusted 95% confidence interval) are from mixed model for repeated measures (MMRM) analysis. In Studies 1 and 6, the primary analysis was not based on MMRM and in Studies 2 and 6 the primary efficacy measure was not based on MADRS

Digit Symbol Substitution Test in Major Depressive Disorder

Two, eight week, randomized, double-blind, placebo-controlled studies were conducted to evaluate the effect of TRINTELLIX on the Digit Symbol Substitution Test (DSST) during the treatment of acute MDD. The DSST is a neuropsychological test that most specifically measures processing speed, an aspect of cognitive function that may be impaired in MDD. Patients are asked to match nine symbols with their corresponding number (1 to 9) according to a key; the score is the correct number of matches achieved in 90 seconds. For reference, the mean score for healthy 45 to 54 year-old subjects is 50 (SD=15).

Study 7 randomized adult patients meeting the diagnostic criteria for recurrent MDD to receive TRINTELLIX 10 mg, TRINTELLIX 20 mg, or placebo once daily. Study 8 randomized adult patients meeting the diagnostic criteria for recurrent MDD and reporting subjective difficulty concentrating or slow thinking to receive a flexible dose of TRINTELLIX (10 or 20 mg) or placebo once daily. Neither study included patients whose MDD was in remission yet who continued to experience difficulty concentrating or slow thinking. Patients' mean age was 46 (SD=12) and 45 (SD=12) in Study 7 and 8, respectively. In both studies, patients in the TRINTELLIX group had a statistically significantly greater improvement in number of correct responses on the DSST (Table 6); depressed mood as assessed by change from baseline in MADRS total score also improved in both studies.

Table 6. Effect of TRINTELLIX on the Digit Symbol Substitution Test (DSST)
Study No. | Treatment Group | Number of Patients | Mean Baseline Score (SD) | LS Mean Change from Baseline (SE) | Placebo-subtracted Difference [Difference (drug minus placebo) in least-squares mean change from baseline.] (95% CI)
Study 7 | TRINTELLIX (10 mg/day) [Doses are statistically significantly superior to placebo.] | 193 | 42.0 (12.6) | 9.0 (0.6) | 4.2 (2.5, 5.9)
Study 7 | TRINTELLIX (20 mg/day) | 204 | 41.6 (12.7) | 9.1 (0.6) | 4.3 (2.6, 5.9)
Study 7 | Placebo | 194 | 42.4 (13.8) | 4.8 (0.6) | --
Study 8 | TRINTELLIX (10/20 mg/day) | 175 | 42.1 (11.9) | 4.6 (0.5) | 1.8 (0.3, 3.2)
Study 8 | Placebo | 167 | 43.0 (12.3) | 2.9 (0.5) | --
SD: standard deviation; SE: standard error; LS Mean: least-squares mean; CI: unadjusted confidence interval.

The effects observed on DSST may reflect improvement in depression. Comparative studies have not been conducted to demonstrate a therapeutic advantage over other antidepressants on the DSST.

Maintenance Studies

In a non-US maintenance study (Study 9 in Figure 6), 639 patients meeting DSM-IV-TR criteria for MDD received flexible doses of TRINTELLIX (5 mg or 10 mg) once daily during an initial 12 week open-label treatment phase; the dose of TRINTELLIX was fixed during Weeks 8 to 12. Three hundred ninety six (396) patients who were in remission (MADRS total score ≤10 at both Weeks 10 and 12) after open-label treatment were randomly assigned to continuation of a fixed dose of TRINTELLIX at the final dose they responded to (about 75% of patients were on 10 mg/day) during the open-label phase or to placebo for 24 to 64 weeks. Approximately 61% of randomized patients satisfied remission criterion (MADRS total score ≤10) for at least four weeks (since Week 8), and 15% for at least eight weeks (since Week 4). Patients on TRINTELLIX experienced a statistically significantly longer time to have recurrence of depressive episodes than did patients on placebo. Recurrence of depressive episode was defined as a MADRS total score ≥22 or lack of efficacy as judged by the investigator.

Figure 6. Kaplan-Meier Estimates of Proportion of Patients with Recurrence (Study 9)

In a U.S.-based maintenance study (Study 10 in Figure 7), 1,106 patients meeting DSM-IV-TR criteria for MDD were treated with a fixed dose of TRINTELLIX 10 mg once daily during an initial 16 week open-label treatment phase. Five hundred and eighty (580) patients who were in remission (MADRS total score ≤12 at both Weeks 14 and 16) after open-label treatment were randomized in a 1:1:1:1 ratio to TRINTELLIX 5 mg/day, 10 mg/day, 20 mg/day, or placebo daily for 32 weeks. The definition of recurrence of depressive episodes was the same as for Study 9. For all three doses of TRINTELLIX evaluated, patients treated with TRINTELLIX experienced a statistically significantly longer time to recurrence of depressive episodes than did patients treated with placebo.

Figure 7. Kaplan-Meier Estimates of Proportion of Patients with Recurrence (Study 10)

Prospective Evaluation of Treatment Emergent Sexual Dysfunction (TESD)

Two, randomized, double-blind, active-controlled studies were conducted to prospectively compare the incidence of TESD between TRINTELLIX and SSRIs via a validated self-rated measure of sexual function, the Changes in Sexual Functioning Questionnaire Short Form (CSFQ-14). The CSFQ-14 is designed to measure illness- and medication-related changes in sexual functioning that consists of 14 items measuring sexual functioning as a total score. The CSFQ-14 consists of subscales that assess the three phases of the sexual response cycle (desire, arousal, and orgasm). Higher scores on the CSFQ-14 indicate greater sexual function and for reference, a 2-3 point change is considered clinically meaningful.

Effect of Switching from SSRI to TRINTELLIX on TESD

The effect of TRINTELLIX on TESD induced by prior SSRI treatment in MDD patients whose depressive symptoms were adequately treated was evaluated in an eight-week, randomized, double-blind, active-controlled (escitalopram), flexible-dose study (Study 11). Patients taking citalopram, sertraline, or paroxetine for at least eight weeks duration and who were experiencing sexual dysfunction attributed to their SSRI treatment were switched to TRINTELLIX (n=217) or escitalopram (n=207). For both TRINTELLIX and escitalopram, patients were started on 10 mg, increased to 20 mg at Week 1, followed by flexible dosing. The majority of subjects received the 20 mg dose of TRINTELLIX (65.6%) or the 20 mg dose of escitalopram (71.9%) during the study.

Improvement in TESD induced by prior SSRI treatment in subjects switched to TRINTELLIX was superior to the improvement observed in those subjects who switched to escitalopram (2.2 point improvement vs escitalopram on the change from Baseline in CSFQ-14 total score, with 95% confidence interval 0.48 – 4.02), after eight weeks of treatment, while both drugs maintained the subjects' prior antidepressant response. For change from Baseline in CSFQ-14, see Figure 8.

Figure 8. Change from Baseline in CSFQ-14 Total Score by Study Visit (Week) in Study 11

Study Visit (Week)

Effects in Healthy Volunteers with Normal Sexual Functioning at Baseline

In a randomized Healthy Volunteer study (Study 12) with 348 subjects aged 18 years to 40 years with normal sexual functioning without the confounding effect of depression, TESD with TRINTELLIX 10 mg (n=85), but not with TRINTELLIX 20 mg (n=91), was statistically significantly less than with paroxetine 20 mg (n=83) [see Adverse Reactions (6.1)]. Paroxetine 20 mg was statistically significantly worse than placebo (n=89), confirming assay sensitivity in this study. For change from Baseline in CSFQ-14, see Figure 9.

Figure 9. Change from Baseline in CSFQ-14 Total Score by Study Visit (Week) in Healthy Volunteers (Study 12)

16 HOW SUPPLIED/STORAGE AND HANDLING

TRINTELLIX tablets are available as follows:

 | Strengths
 | 10 mg | 20 mg
Color | yellow | red
Debossment | "10" on one side of tablet | "20" on one side of tablet
 | "TL" on other side of tablet | "TL" on other side of tablet
Presentations and NDC Codes | Bottles of approximately 2520 film-coated tablets, NDC 55154-0256-8 | Bottles of approximately 2430 film-coated tablets, NDC 55154-0257-8

STORAGE AND HANDLING

Store at 77°F (25°C); excursions permitted to 59°F to 86°F (15°C to 30°C) [see USP Controlled Room Temperature].

17 PATIENT COUNSELING INFORMATION

Advise the patient to read the FDA-approved patient labeling (Medication Guide).

Suicidal Thoughts and Behaviors

Advise patients and caregivers to look for the emergence of suicidal ideation and behavior, especially early during treatment and when the dose is adjusted up or down, and instruct them to report such symptoms to the healthcare provider [see Boxed Warning, Warnings and Precautions (5.1)].

Concomitant Medication

Advise patients to inform their healthcare provider if they are taking, or plan to take, any prescription or over-the-counter medications because of a potential for interactions. Instruct patients not to take TRINTELLIX with an MAOI or within 14 days of stopping an MAOI and to allow 21 days after stopping TRINTELLIX before starting an MAOI [see Dosage and Administration (2.4), Contraindications (4), Warnings and Precautions (5.2), Drug Interactions (7.1)].

Serotonin Syndrome

Caution patients about the risk of serotonin syndrome, particularly with the concomitant use of TRINTELLIX and triptans, tricyclic antidepressants, opioids, lithium, tryptophan supplements, busipirone, and St. John's Wort and with drugs that impair metabolism of serotonin (in particular, MAOIs, both those intended to treat psychiatric disorders and also others, such as linezolid) [see Warnings and Precautions (5.2), Drug Interactions (7.1, 7.2)]. Instruct patients to contact their health care provider or report to the emergency room if they experience signs or symptoms of serotonin syndrome.

Increased Risk of Bleeding

Inform patients about the concomitant use of TRINTELLIX with NSAIDs, aspirin, warfarin, or other drugs that affect coagulation because combined use has been associated with an increased risk of bleeding. Advise patients to inform their health care provider if they are taking or planning to take any prescription or over-the-counter medications that increase the risk of bleeding [see Warnings and Precautions (5.3)].

Activation of Mania/Hypomania

Advise patients and their caregivers to look for signs of activation of mania/hypomania [see Warnings and Precautions (5.4)].

Discontinuation of Treatment

Advise patients not to abruptly stop taking TRINTELLIX without first talking to their healthcare provider. Patients should be aware that discontinuation effects may occur when stopping TRINTELLIX and they should monitor for discontinuation symptoms [see Warnings and Precautions (5.5) and Adverse Reactions (6.1)].

Angle Closure Glaucoma

Patients should be advised that taking TRINTELLIX can cause mild pupillary dilation, which in susceptible individuals, can lead to an episode of angle closure glaucoma. Pre-existing glaucoma is almost always open-angle glaucoma because angle closure glaucoma, when diagnosed, can be treated definitively with iridectomy. Open-angle glaucoma is not a risk factor for angle closure glaucoma. Patients may wish to be examined to determine whether they are susceptible to angle closure, and have a prophylactic procedure (e.g., iridectomy), if they are susceptible [see Warnings and Precautions (5.6)].

Hyponatremia

Advise patients that if they are treated with diuretics, or are otherwise volume depleted, or are elderly, they may be at greater risk of developing hyponatremia while taking TRINTELLIX [see Warnings and Precautions (5.7)].

Sexual Dysfunction

Advise patients that use of TRINTELLIX may cause symptoms of sexual dysfunction in both male and female patients. Inform patients that they should discuss any changes in sexual function and potential management strategies with their healthcare provider [see Warnings and Precautions (5.8)].

Nausea

Advise patients that nausea is one of the most common adverse reactions, and is dose related. Nausea commonly occurs within the first week of treatment, then decreases in frequency but can persist in some patients [see Adverse Reactions (6.1)].

Allergic Reactions

Advise patients to notify their healthcare provider if they develop an allergic reaction such as rash, hives, swelling, or difficulty breathing.

Pregnancy

Advise a pregnant woman or a woman planning to become pregnant that TRINTELLIX may cause withdrawal symptoms in the newborn or persistent pulmonary hypertension of the newborn (PPHN) [see Use in Specific Populations (8.1)]. Advise the patients that there is a pregnancy exposure registry that monitors pregnancy outcomes in women exposed to TRINTELLIX during pregnancy [see Use in Specific Populations (8.1)].

Distributed and marketed by:
Takeda Pharmaceuticals America, Inc.
Cambridge, MA 02142

TRINTELLIX is a trademark of H. Lundbeck A/S registered with the U.S. Patent and Trademark Office and used under license by Takeda Pharmaceuticals America, Inc.

©2025 Takeda Pharmaceuticals America, Inc. All rights reserved.

Distributed By:

Cardinal Health

Dublin, OH 43017

ER7274D Rev. C

ER7275 Rev. B

LUN205 R26

MEDICATION GUIDE
TRINTELLIX® (trin'-TELL-ix)
(vortioxetine)
Tablets

What is the most important information I should know about TRINTELLIX?

TRINTELLIX can cause serious side effects, including:

- Increased risk of suicidal thoughts and actions. TRINTELLIX and other antidepressant medicines increase the risk of suicidal thoughts and actions in people 24 years of age and younger, especially within the first few months of treatment or when the dose is changed. TRINTELLIX is not for use in children.
  - Depression or other mental illnesses are the most important causes of suicidal thoughts or actions.
  How can I watch for and try to prevent suicidal thoughts and actions?
  1. Pay close attention to any changes, especially sudden changes in mood, behavior, thoughts, or feelings, of if you develop suicidal thoughts or actions. This is very important when an antidepressant medicine is started or when the dose is changed.
  2. Call your healthcare provider right away to report new or sudden changes in mood, behavior, thoughts, or feelings or if you develop suicidal thoughts or actions.
  3. Keep all follow-up visits with your healthcare provider as scheduled. Call your healthcare provider between visits as needed, especially if you have concerns about symptoms.

Call your healthcare provider or get emergency help right away if you have any of the following symptoms, especially if they are new, worse, or worry you:

- attempts to commit suicide
- thoughts about suicide or dying
- feeling agitated, restless, angry or irritable
- other unusual changes in behavior or mood

- acting on dangerous impulses
- new or worse depression
- trouble sleeping

- acting aggressive or violent
- new or worse anxiety or panic attacks
- an increase in activity or talking more than what is normal for you

What is TRINTELLIX?

TRINTELLIX is a prescription medicine used in adults to treat a certain type of depression called Major Depressive Disorder (MDD).
TRINTELLIX has not been shown to be safe and effective for use in children.

Do not take TRINTELLIX if you:

- are allergic to vortioxetine or any of the ingredients in TRINTELLIX. See the end of this Medication Guide for a complete list of ingredients in TRINTELLIX
- are taking, or have stopped taking within the last 14 days, a medicine called a Monoamine Oxidase Inhibitor (MAOI), including the antibiotic linezolid or intravenous methylene blue

Ask your healthcare provider or pharmacist if you are not sure if you take an MAOI, including the antibiotic linezolid or intravenous methylene blue.

Do not start taking an MAOI for at least 21 days after you stop treatment with TRINTELLIX.

Before taking TRINTELLIX, tell your healthcare provider about all your medical conditions, including if you:

- have or had bleeding problems
- have, or have a family history of, bipolar disorder, mania, or hypomania
- have high pressure in the eye (glaucoma)
- have low sodium levels in your blood
- are pregnant or plan to become pregnant. TRINTELLIX may harm your unborn baby. Taking TRINTELLIX during your third trimester of pregnancy may cause your baby to have withdrawal symptoms after birth or may cause your baby to be at increased risk for a serious lung problem at birth. Talk to your healthcare provider about the risks to you and your unborn or newborn baby if you take TRINTELLIX during pregnancy.
  - Tell your healthcare provider right away if you become pregnant or think you are pregnant during treatment with TRINTELLIX.
  - There is a pregnancy registry for females who are exposed to TRINTELLIX during pregnancy. The purpose of the registry is to collect information about the health of females exposed to TRINTELLIX and their baby. If you become pregnant during treatment with TRINTELLIX, talk to your healthcare provider about registering with the National Pregnancy Registry for Antidepressants at 1-844-405-6185 or visit online at https://womensmentalhealth.org/clinical-and-research-programs/pregnancyregistry/antidepressants/.
- are breastfeeding or plan to breastfeed. It is not known if TRINTELLIX passes into your breast milk. Talk to your healthcare provider about the best way to feed your baby during treatment with TRINTELLIX.

Tell your healthcare provider about all the medicines you take, including prescription and over-the-counter medicines, vitamins, and herbal supplements.

TRINTELLIX and some other medicines may affect each other causing possible serious side effects. TRINTELLIX may affect the way other medicines work and other medicines may affect the way TRINTELLIX works.

Especially tell your healthcare provider if you take:

- medicines used to treat migraine headache called triptans
- tricyclic antidepressants
- lithium
- tramadol, fentanyl, meperidine, methadone, or other opioids
- tryptophan
- buspirone
- St. John's Wort
- medicines that can affect blood clotting such as aspirin, nonsteroidal anti-inflammatory drugs (NSAIDs), warfarin
- diuretics
- medicines used to treat mood, anxiety, psychotic or thought disorders, including selective serotonin reuptake inhibitors (SSRIs) and serotonin norepinephrine reuptake inhibitors (SNRIs)
- medicines used to treat seizures or convulsions

Ask your healthcare provider if you are not sure if you are taking any of these medicines. Your healthcare provider can tell you if it is safe to take TRINTELLIX with your other medicines.

Do not start or stop any other medicines during treatment with TRINTELLIX without talking to your healthcare provider first. Stopping TRINTELLIX suddenly may cause you to have serious side effects. See, "What are the possible side effects of TRINTELLIX?"

Know the medicines you take. Keep a list of them to show to your healthcare provider and pharmacist when you get a new medicine.

How should I take TRINTELLIX?

- Take TRINTELLIX exactly as your healthcare provider tells you to take it. Your healthcare provider may need to change the dose of TRINTELLIX until it is the right dose for you.
- Take TRINTELLIX 1 time each day.
- Take TRINTELLIX with or without food.
- If you take too much TRINTELLIX, call your Poison Help Line at 1-800-222-1222 or go to the nearest hospital emergency room right away.

What are the possible side effects of TRINTELLIX?

TRINTELLIX may cause serious side effects, including:

- See, "What is the most important information I should know about TRINTELLIX?"
- Serotonin syndrome. A potentially life-threatening problem called serotonin syndrome can happen when you take TRINTELLIX with certain other medicines. See, " Do not take TRINTELLIX if you ". Call your healthcare provider or go to the nearest hospital emergency room right away if you have any of the following signs and symptoms of serotonin syndrome:

- agitation
- seeing or hearing things that are not real (hallucinations)
- confusion
- coma
- fast heart-beat
- changes in blood pressure
- dizziness

- sweating
- flushing
- high body temperature (hyperthermia)
- shaking (tremors), stiff muscles, or muscle twitching
- loss of coordination
- seizures
- nausea, vomiting, diarrhea

- Increased risk of bleeding. Taking TRINTELLIX with aspirin, non-steroidal anti-inflammatory drugs (NSAIDs), warfarin or blood thinners may add to this risk. Tell your healthcare provider right away about any unusual bleeding or bruising.
- Manic episodes. Manic episodes may happen in people with bipolar disorder who take TRINTELLIX. Symptoms may include:

- greatly increased energy
- racing thoughts
- unusually grand ideas
- talking more or faster than usual

- severe problems sleeping
- reckless behavior
- excessive happiness or irritability

- Discontinuation syndrome. Suddenly stopping TRINTELLIX may cause you to have serious side effects. Your healthcare provider may want to decrease your dose slowly. Symptoms may include:

- nausea
- sweating
- changes in your mood
- irritability and agitation
- dizziness

- electric shock feeling (paresthesia)
- tremor
- anxiety
- confusion
- headache

- tiredness
- problems sleeping
- hypomania
- ringing in your ears (tinnitus)
- seizures

- Eye problems (angle-closure glaucoma). TRINTELLIX may cause a type of eye problem called angle-closure glaucoma in people with certain other eye conditions. You may want to undergo an eye examination to see if you are at risk and receive preventative treatment if you are. Call your healthcare provider if you have eye pain, changes in your vision, or swelling or redness in or around the eye.
- Low levels of sodium in your blood (hyponatremia). Low sodium levels in your blood that may be serious and may cause death, can happen during treatment with TRINTELLIX. Elderly people and people who take certain medicines may be at a greater risk for developing low sodium levels in your blood. Signs and symptoms may include:

- headache
- difficulty concentrating
- memory changes

- confusion
- weakness and unsteadiness on your feet, which can lead to falls

In more severe or more sudden cases, signs and symptoms include:

- seeing or hearing things that are not real (hallucinations)
- fainting
- seizures

- coma
- stopping breathing (respiratory arrest)

- Sexual problems (dysfunction). Taking TRINTELLIX may cause sexual problems.
  Symptoms in males may include:

- delayed ejaculation or inability to have an ejaculation
- problems getting or keeping an erection

- decreased sex drive

Symptoms in females may include:

- decreased sex drive

- delayed orgasm or inability to have an orgasm

Talk to your healthcare provider if you develop any changes in your sexual function or if you have any questions or concerns about sexual problems during treatment with TRINTELLIX. There may be treatments your healthcare provider can suggest.

The most common side effects of TRINTELLIX include nausea, constipation, and vomiting.
These are not all the possible side effects of TRINTELLIX.

Call your doctor for medical advice about side effects. You may report side effects to FDA at 1-800-FDA-1088.

How should I store TRINTELLIX?

- Store TRINTELLIX at room temperature between 68°F to 77°F (20°C to 25°C).
- Keep TRINTELLIX and all medicines out of the reach of children.

General information about the safe and effective use of TRINTELLIX.

Medicines are sometimes prescribed for purposes other than those listed in a Medication Guide. Do not take TRINTELLIX for a condition for which it was not prescribed. Do not give TRINTELLIX to other people, even if they have the same symptoms that you have. It may harm them. You can ask your pharmacist or healthcare provider for information about TRINTELLIX that is written for health professionals.

What are the ingredients in TRINTELLIX?
Active ingredient: vortioxetine hydrobromide
Inactive ingredients: mannitol, microcrystalline cellulose, hydroxypropyl cellulose, sodium starch glycolate, magnesium stearate and film coating consisting of hypromellose, titanium dioxide, polyethylene glycol 400, iron oxide red (5 mg and 20 mg), and iron oxide yellow (10 mg)
Distributed and Marketed by:
Takeda Pharmaceuticals America, Inc. Cambridge, MA 02142
TRINTELLIX is a trademark of H. Lundbeck A/S registered with the U.S. Patent and Trademark Office and used under license by Takeda Pharmaceuticals America, Inc.
©2025 Takeda Pharmaceuticals America, Inc. All rights reserved.
For more information, go to www.TRINTELLIX.com or call 1-877-TAKEDA-7 (1-877-825-3327).

Distributed By:

Cardinal Health

Dublin, OH 43017

ER7274D Rev. C

ER7275 Rev. B

This Medication Guide has been approved by the U.S. Food and Drug Administration.

Revised: 2/2025

Package/Label Display Panel

Contains Approximately

2520 Tablets

TRINTELLIX

vortioxetine tablets

10 mg*

*Each yellow tablet contains:

12.71 mg vortioxetine hydrobromide

(equivalent to 10 mg vortioxetine).

Rx Only

WARNING: Keep out of reach of

children.

Package/Label Display Panel

Contains Approximately

2430 Tablets

TRINTELLIX

vortioxetine tablets

20 mg*

*Each red tablet contains:

25.42 mg vortioxetine hydrobromide

(equivalent to 20 mg vortioxetine).

Rx Only

WARNING: Keep out of reach of

children.